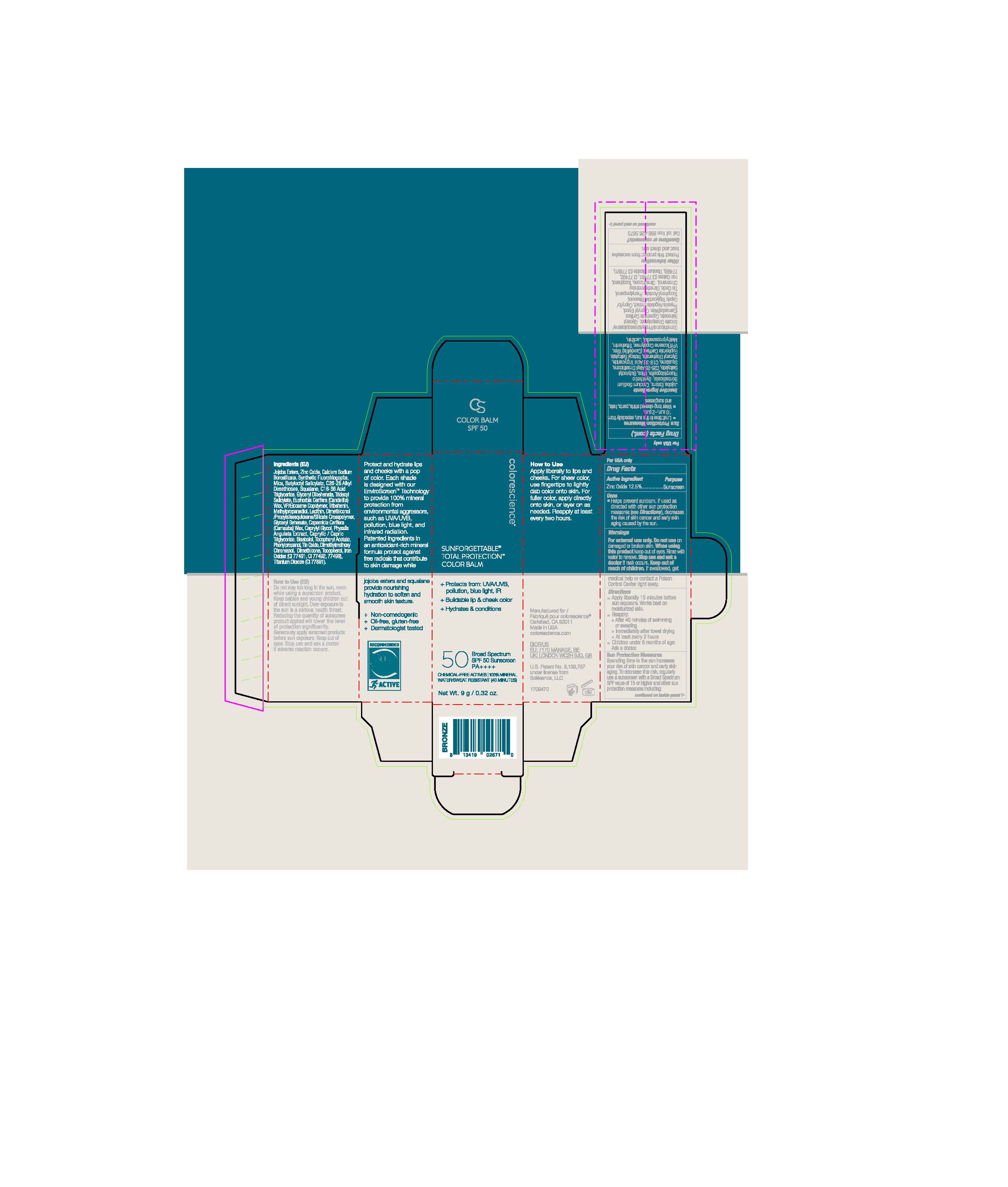 DRUG LABEL: Sunforgettable Total Protection Color Balm (Bronze)
NDC: 68078-035 | Form: STICK
Manufacturer: Colorescience
Category: otc | Type: HUMAN OTC DRUG LABEL
Date: 20251015

ACTIVE INGREDIENTS: ZINC OXIDE 125 mg/1 g
INACTIVE INGREDIENTS: TITANIUM DIOXIDE; CAPRYLYL GLYCOL; METHYLPROPANEDIOL; PHENYLPROPANOL; C18-36 ACID TRIGLYCERIDE; .ALPHA.-BISABOLOL, (+/-)-; MICA; TOCOPHEROL; VINYLPYRROLIDONE/EICOSENE COPOLYMER; DIMETHICONE; CARNAUBA WAX; DIMETHICONOL/PROPYLSILSESQUIOXANE/SILICATE CROSSPOLYMER (450000000 MW); DIMETHYLMETHOXY CHROMANOL; TRIDECYL SALICYLATE; LECITHIN, SOYBEAN; SQUALANE; BUTYLOCTYL SALICYLATE

Sunforgettable Total Protection Color Balm (Bronze)